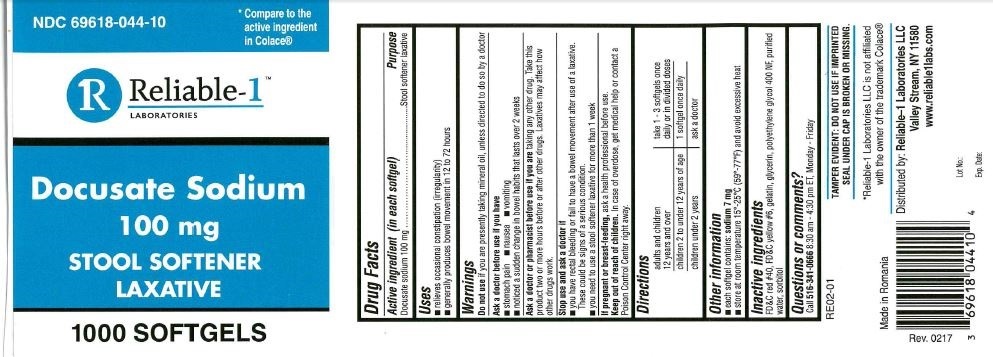 DRUG LABEL: Docusate Sodium
NDC: 69618-044 | Form: CAPSULE
Manufacturer: Reliable-1 Laboratories LLC
Category: otc | Type: HUMAN OTC DRUG LABEL
Date: 20220817

ACTIVE INGREDIENTS: DOCUSATE SODIUM 100 mg/1 1
INACTIVE INGREDIENTS: WATER; SORBITOL; POLYETHYLENE GLYCOL 400; FD&C RED NO. 40; GLYCERIN; FD&C YELLOW NO. 6; GELATIN

Docusate Sodium 100 mg

Drug Facts

Active ingredient (in each softgel)

Docusate sodium 100 mg

Purpose

Stool softener laxative

Uses

- relieves occasional constipation (irregularity)
- generally produces bowel movement in 12 to 72 hours

Warnings

Do not use if you are presently taking mineral oil, unless directed to do so by a doctor

Ask a doctor before use if you have

- stomach pain
- nausea
- vomiting
- noticed a sudden change in bowel habits that lasts over 2 weeks

Ask a doctor or pharmacist before use if you are taking any other drug. Take this product two or more hours before or after other drugs. Laxatives may affect how other drugs work.

Stop use and ask a doctor if

- you have rectal bleeding or fail to have a bowel movement after use of a laxative. These could be signs of a serious condition.
- you need to use stool softner laxative for more than 1 week

PREGNANCY OR BREAST FEEDING

If pregnant or breast-feeding, ask a health professional before use.

Keep out of reach of children. In case of overdose, get medical help or contact a Poison Control Center right away.

Directions

adults and children 12 years and over | take 1 - 3 softgels once daily or in divded doses
children 2 to under 12 years of age | 1 softgel once daily
children under 2 years | ask a doctor

Other information

- each softgel contains: s odium 7 mg
- store at room temperature 15º-25ºC (59º-77ºF) and avoid excessive heat

Inactive ingredients

FD&C red #40, FD&C yellow #6, gelatin, glycerin, polyethylene glycol 400 NF, purified water, sorbitol

Questions or comments? Call 516-341-0666 8:30 am - 4:30 pm ET, Monday - Friday

TAMPER EVIDENT: DO NOT USE IF IMPRINTED SEAL UNDER CAP IS BROKEN OR MISSING.

*Reliable-1 Laboratories LLC is not affiliated with the owner of the trademark Colace®

Distributed by: Reliable-1 Laboratories LLC Valley Stream, NY 11580

www.reliable1labs.com

Made in Romania

PACKAGE LABEL

NDC 69618-044-10

*Compare to the active ingredient in Colace®

Reliable-1™ LABORATORIES

Docusate Sodium 100 mg

STOOL SOFTENER LAXATIVE

1000 SOFTGELS